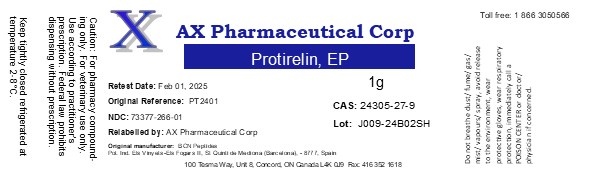 DRUG LABEL: Protirelin
NDC: 73377-266 | Form: POWDER
Manufacturer: AX Pharmaceutical Corp
Category: other | Type: BULK INGREDIENT - ANIMAL DRUG
Date: 20240412

ACTIVE INGREDIENTS: PROTIRELIN 1 g/1 g

Protirelin